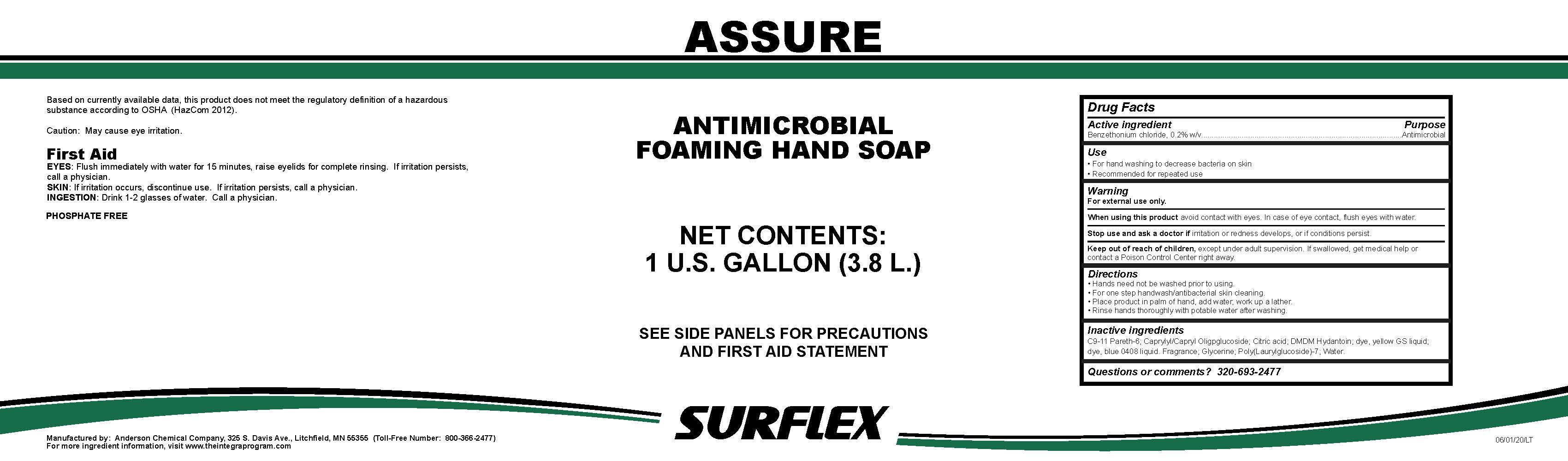 DRUG LABEL: Assure
NDC: 63131-1132 | Form: LIQUID
Manufacturer: Anderson Chemical Company
Category: otc | Type: HUMAN OTC DRUG LABEL
Date: 20200520

ACTIVE INGREDIENTS: BENZETHONIUM CHLORIDE 2 mg/1 mL
INACTIVE INGREDIENTS: DMDM HYDANTOIN; C9-11 PARETH-6; CAPRYLYL/CAPRYL OLIGOGLUCOSIDE; GLYCERIN; POLY(LAURYLGLUCOSIDE)-7; WATER; ANHYDROUS CITRIC ACID; BENZYL ALCOHOL; FD&C YELLOW NO. 5; FD&C BLUE NO. 1

Active ingredient

Benzethonium chloride 0.2% w/v

Purpose

Antimicrobial

Use

- For hand washing to decrease bacterial on skin.
- Recommended for repeated use.

Warning

For external use only.

When using this product avoid contact with eyes. In case of eye contact, flush eyes with water.

Stop use and ask a doctor if irritation or redness develops, or if conditions persist.

Keep out of reach of children, except under adult supervision. If swallowed, get medical help or contact a Poison Control Center.

Directions

- Hands need not be washed prior to using.
- For one step handwash/antibacterial skin cleaning.
- Place product in palm of hand, add water, work up a lather.
- Rinse hands thoroughly with potable water after washing.

Inactive ingredients

C9-11 Pareth-6; Caprylyl/Capryl Oligpglucoside; Citric acid; DMDM Hydantoin; Dye; Fragrance; Glycerine; Poly(Laurylglucoside)-7; Water.

Questions or comments?

320-693-2477